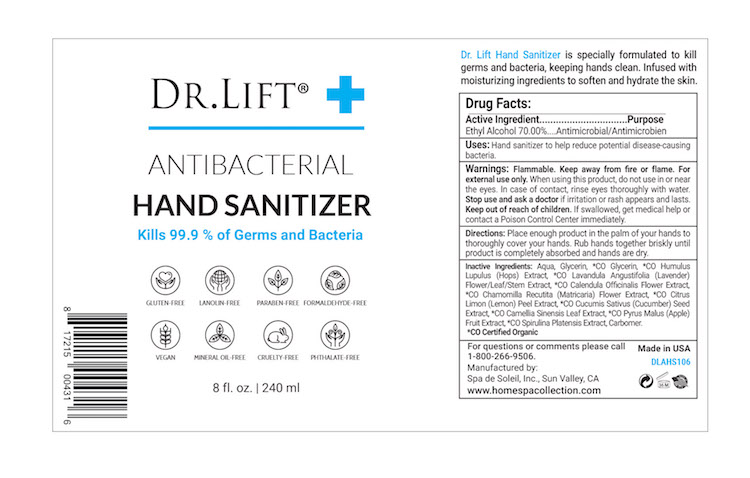 DRUG LABEL: Dr Lift Antibacterial Hand Sanitizer
NDC: 68062-2250 | Form: GEL
Manufacturer: Spa de Soleil
Category: otc | Type: HUMAN OTC DRUG LABEL
Date: 20251112

ACTIVE INGREDIENTS: ALCOHOL 168 mL/240 mL
INACTIVE INGREDIENTS: WATER; XANTHAN GUM; GLYCERIN

Dr Lift Antibacterial Hand Sanitizer

Active Ingredient

Ethyl Alcohol 70.0 %

Purpose

Antimicrobial

Warnings

Flammable. Keep away from fire or flame. For external use only.

When using this product do not use in or near the eyes.

In case of contact, rinse eyes thoroughly with water.

Stop use and ask a doctor if irritation or rash appears and lasts.

Keep out of reach of children. If swallowed, get medical help or contact a Poison Control Center right away.

Keep out of reach of children.

Directions

Place enough product in the palm of your hands to thoroughly cover your hands. Rub hands together briskly until product is completely absorbed and hands are dry.

DOSAGE AND ADMINISTRATION

Place enough product in the palm of your hands to thoroughly cover you hands. Rub hands together briskly until product is completely absorbed and hands are dry.

Inactive Ingredients:

Inactive Ingredients

Aqua, Glycerin, *CO Glycerin, *CO Humulus Lupulus (Hops) Extract, *CO Lavandula Angustifolia (Lavender) Flower/Leaf/Stem Extract, *CO Calendula Officinalis Flower Extract, *CO Chamomilla Recutita (Matricaria) Flower Extract, *CO Citrus Limon (Lemon) Peel Extract, *CO Cucumis Sativus (Cucumber) Seed Extract, *CO Camellia Sinensis Leaf Extract, *CO Pyrus Malus (Apple) Fruit Extract, *CO Spirulina Platensis Extract, Xanthan Gum.

*CO Certified Organic